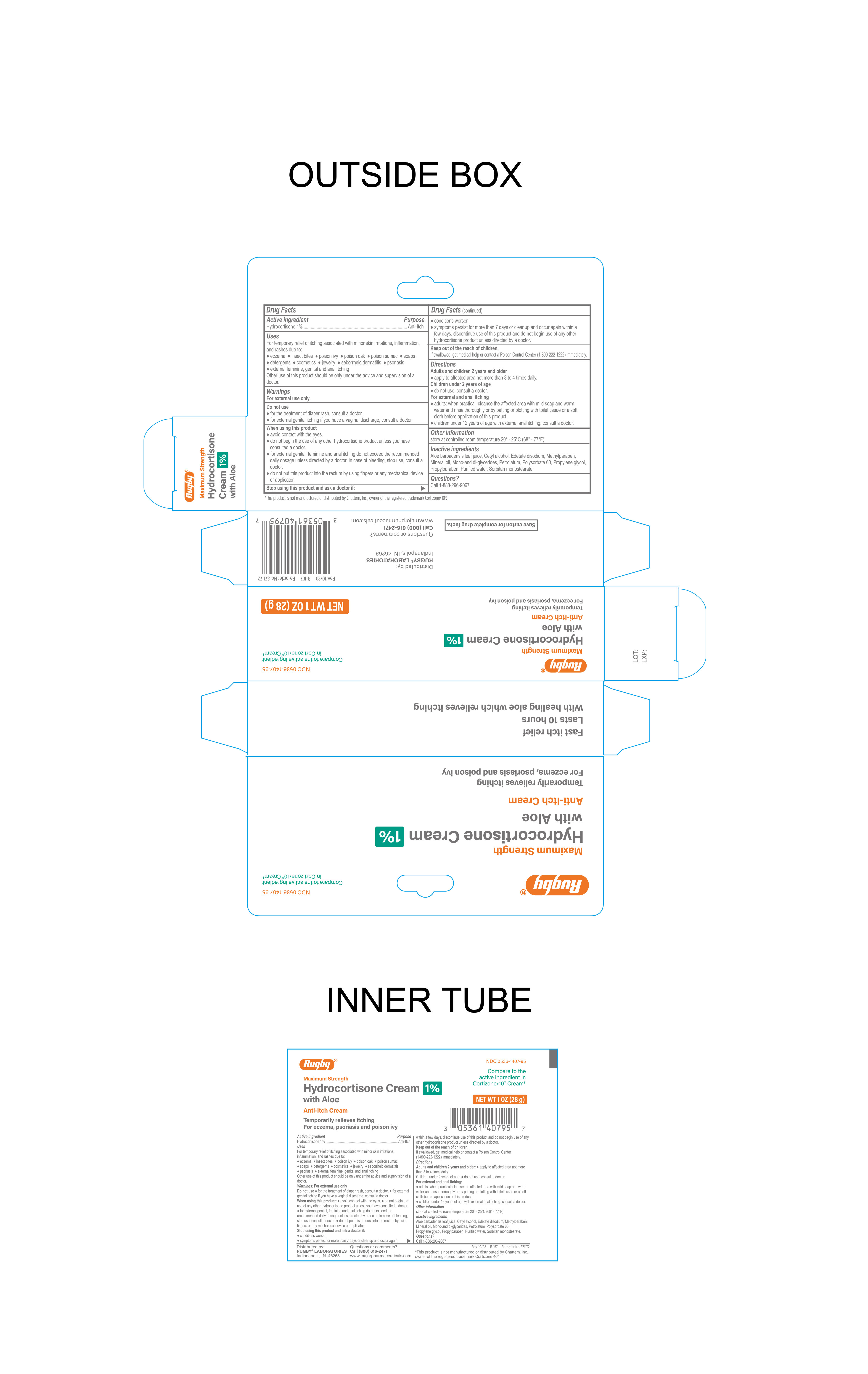 DRUG LABEL: Hydrocortisone Cream with Aloe
NDC: 0536-1407 | Form: CREAM
Manufacturer: Rugby Laboratories
Category: otc | Type: HUMAN OTC DRUG LABEL
Date: 20241220

ACTIVE INGREDIENTS: HYDROCORTISONE 1 g/100 g
INACTIVE INGREDIENTS: GLYCERYL MONO AND DIPALMITOSTEARATE; EDETATE DISODIUM; PROPYLPARABEN; SORBITAN MONOSTEARATE; PROPYLENE GLYCOL; PETROLATUM; ALOE VERA LEAF; CETYL ALCOHOL; WATER; METHYLPARABEN; POLYSORBATE 60; MINERAL OIL

Rugby Hydrocortisone Cream 1% with Aloe

Active Ingredient

Hydrocortisone 1%

Purpose

Anti-Itch

Uses

For temporary relief of itching associated with minor skin irritations, inflammation and rashes due to:

- eczema
- seborrheic dermatitis
- psoriasis
- insect bites
- poison ivy, oak, sumac
- soaps
- detergents
- cosmetics
- jewelry
- external feminine, genital and anal itching

Other uses of this product should be only under the advice and supervision of a doctor.

Keep out of reach of children

If swallowed, get medical help or contact a Poison Control Center (1-800-222-1222) immediately.

Warnings

- for external use only
- avoid contact with eyes
- do not put this product into the rectum by using fingers or any mechanical device or applicator

For External Anal Itching Users:

- do not exceed the recommended daily dosage unless directed by a doctor
- in case of bleeding, consult a doctor promptly
- children under 12 years of age: consult a doctor

Before using any medication, read all label directions. Keep this carton as it contains important information

Do Not Use

- For the treatment of diaper rash, consult a doctor
- For the external genital itching if you have a vaginal discharge, consult a doctor

Stop using this product and ask a doctor if

- Conditions worsen
- symptoms persist for more than 7 days or clear up and occur again within a few days, discontinue use of this product and do not begin use of any other hydrocortisone product unless directed by a doctor.

When using this product

- avoid contact with the eyes.
- do not begin the use of any other hydrocortisone product unless you have consulted a doctor
- for external genital, feminine and anal itching do not exceed the recommended daily dosage unless directed by a doctor. In case of bleeding, stop use, consult a doctor.
- do not put this product into the rectum by using fingers or any mechanical device or applicator.

Directions

Adults and children 2 years and older

- apply to affected area not more than 3 to 4 times daily.

Children under 2 years of age

- Do not use, consult a doctor

For External and anal itching

- When practical, cleanse the affected area with mild soap and warm water and rinse thoroughly

by patting or blotting with toilet tissue or a soft cloth before application of this product.

- adults and children 12 years of age and older, apply to the affected area not more than 3 to 4 times daily
- children under 12 years of age with external anal itching: consult a doctor.

Inactive Ingredients

Aloe barbadensis leaf juice, Cetyl alcohol, Edetate Disodium, Methylparaben, Mineral Oil, Mono and di glycerides, petrolatum, Polysorbate 60, Propylene glycol, propylparaben, purified water, sorbitan monostearate.

Other Information

- store at controlled room temperature 20°-25°C (68°-77°F)

Other Information

Distributed By:

Rugby Laboratories®

Indianapolis, IN 46268

www.majorpharmaceuticals.com

1-800-616-2471

This product is not manufactured or distributed by Chattem, Inc. owner of the registered trademark Cortizone 10®